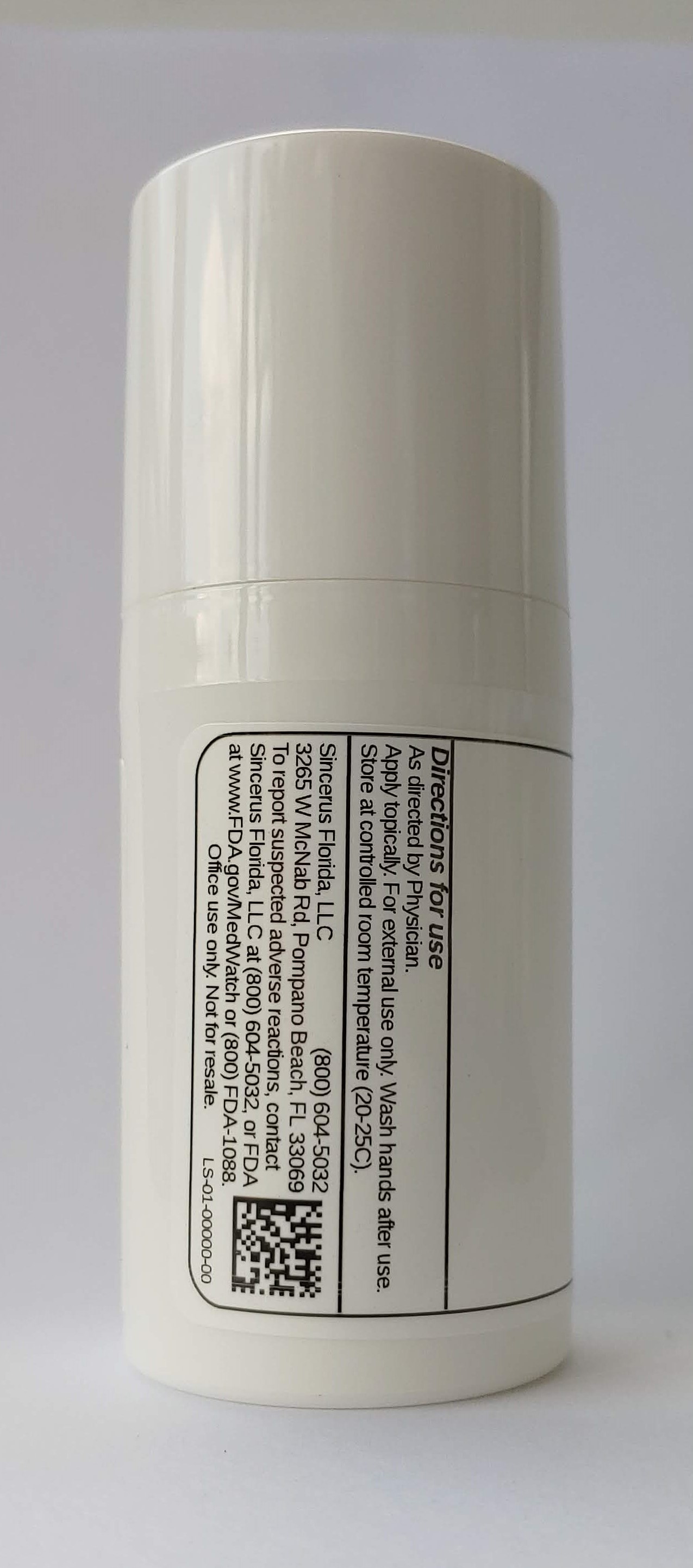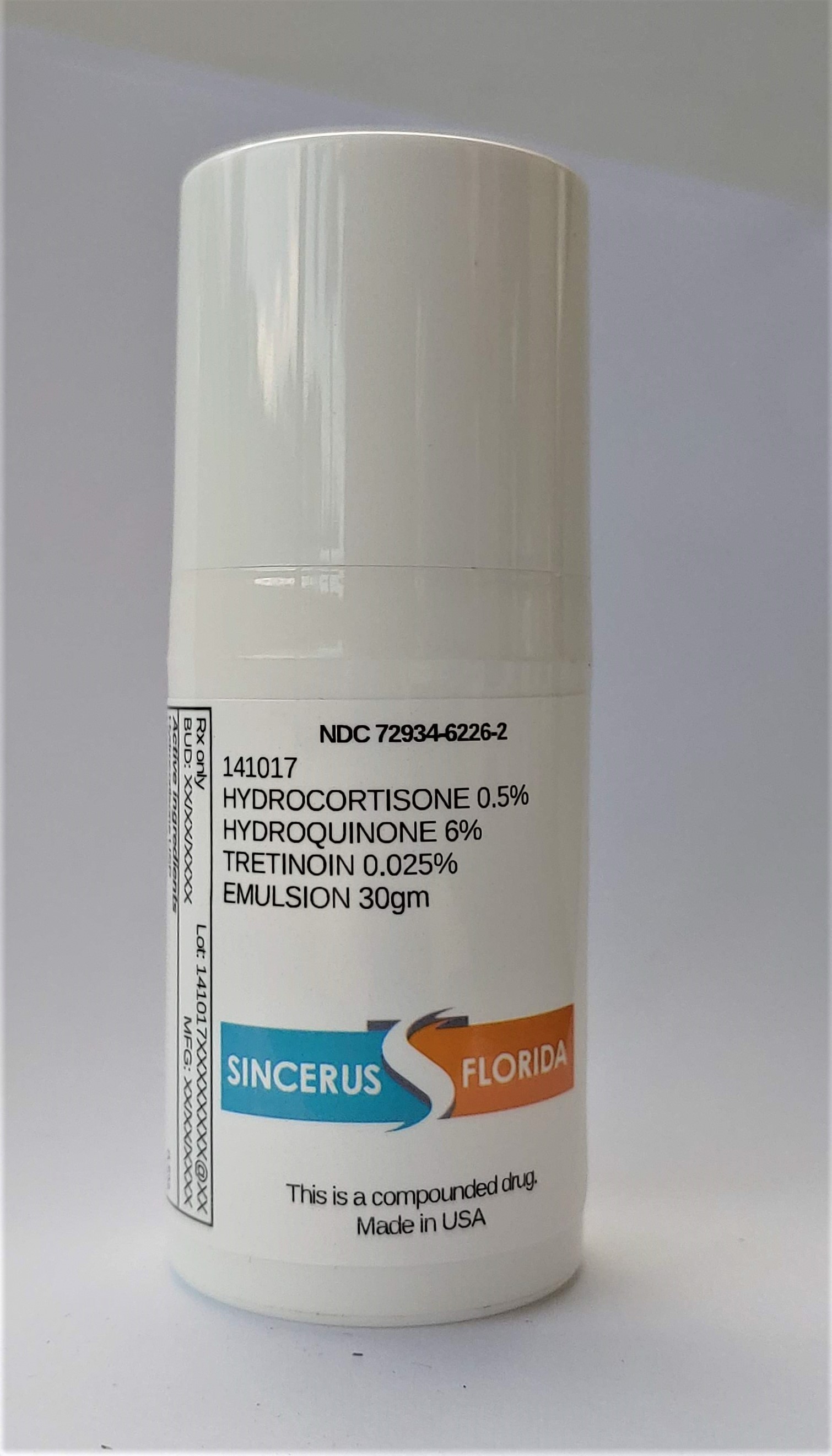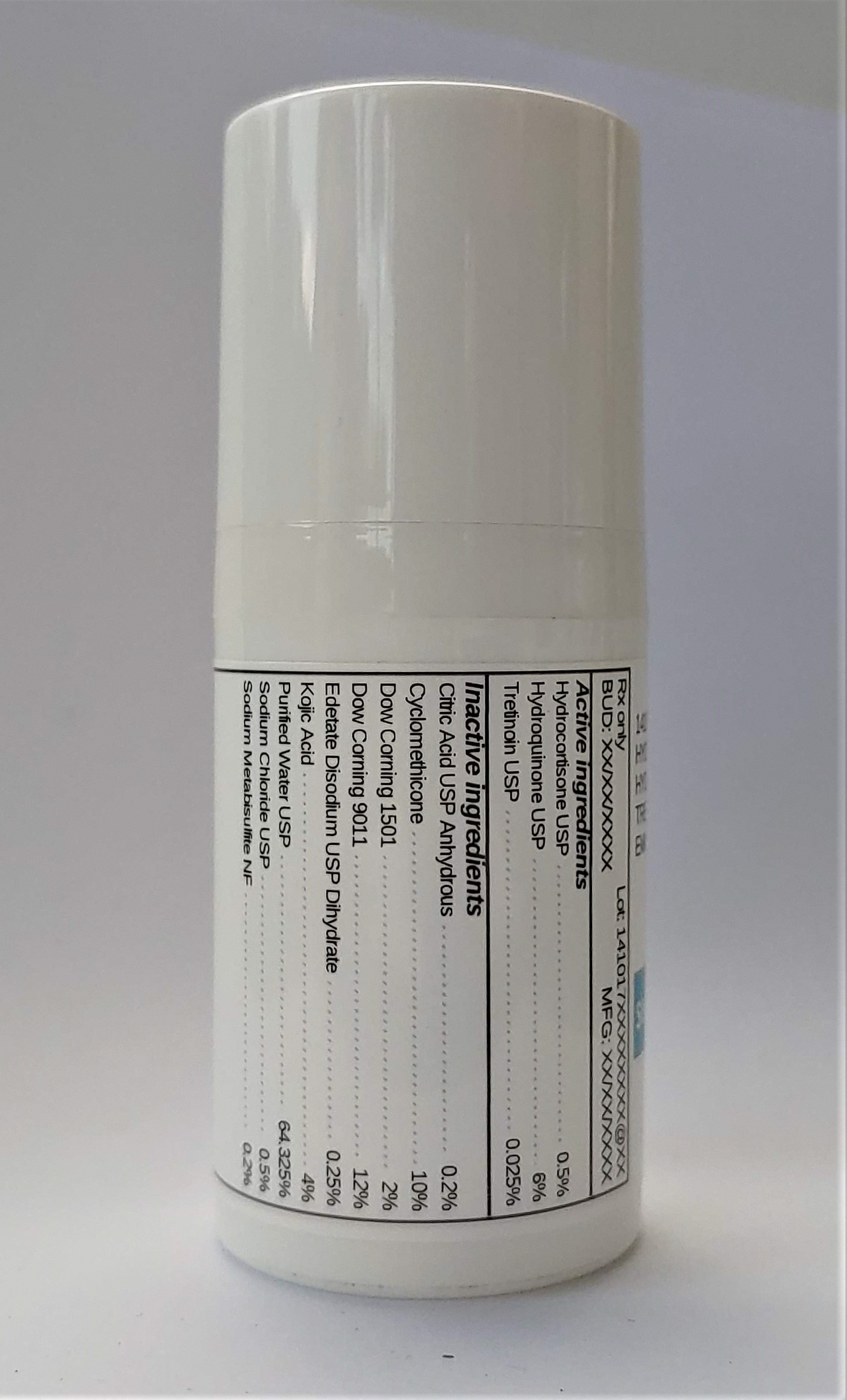 DRUG LABEL: 141017 HYDROCORTISONE 0.5% / HYDROQUINONE 6% / TRETINOIN 0.025%
NDC: 72934-6226 | Form: EMULSION
Manufacturer: Sincerus Florida, LLC
Category: prescription | Type: HUMAN PRESCRIPTION DRUG LABEL
Date: 20200702

ACTIVE INGREDIENTS: HYDROCORTISONE 0.5 g/100 g; HYDROQUINONE 6 g/100 g; TRETINOIN 0.025 g/100 g

141017 HYDROCORTISONE 0.5% / HYDROQUINONE 6% / TRETINOIN 0.025%